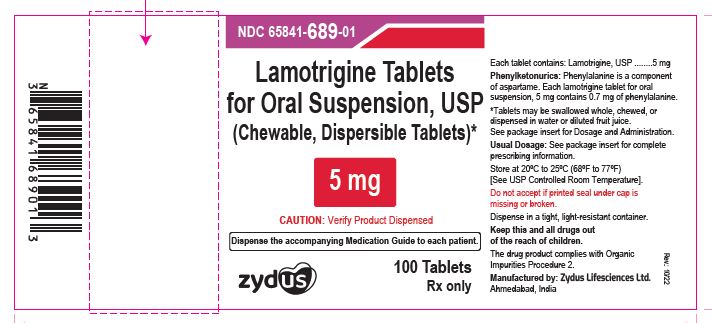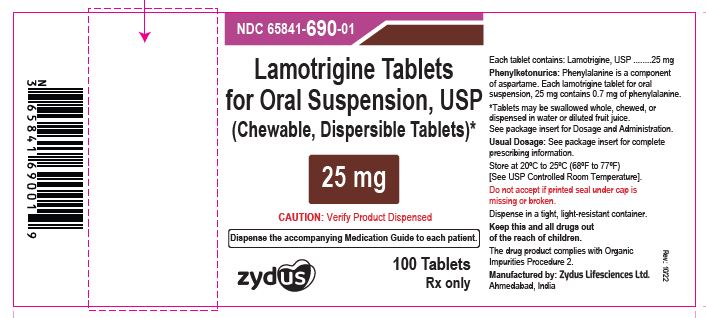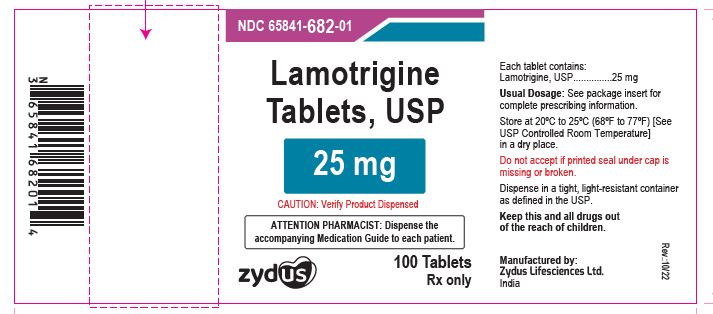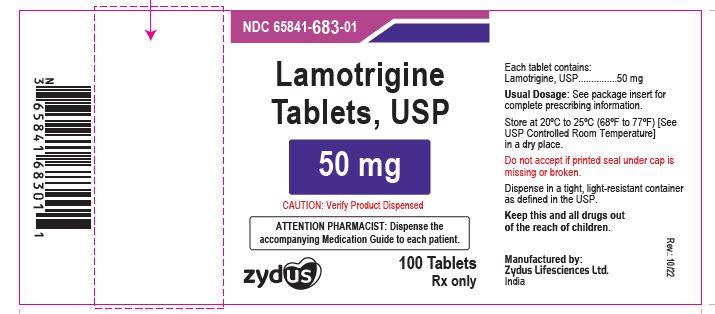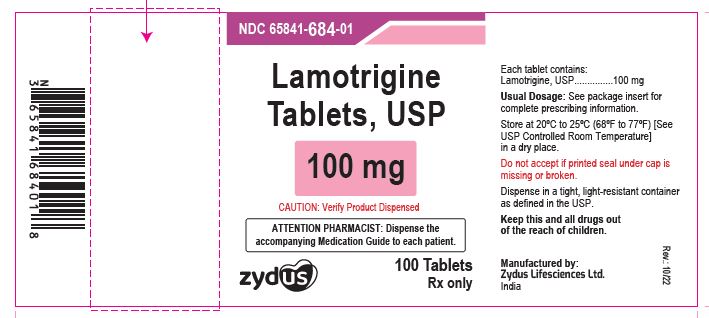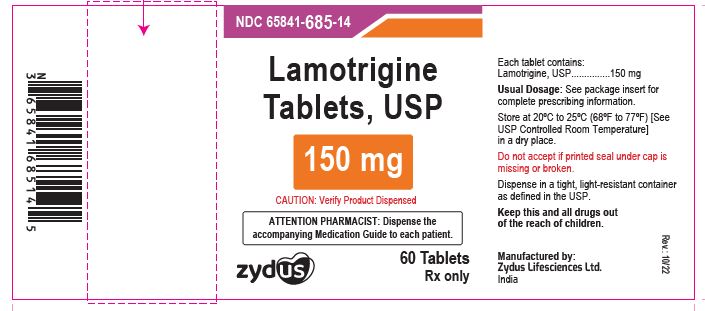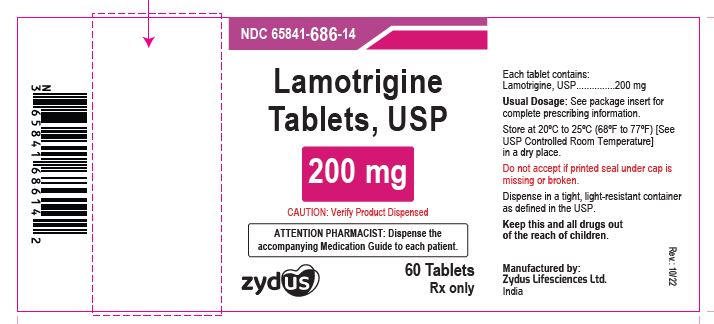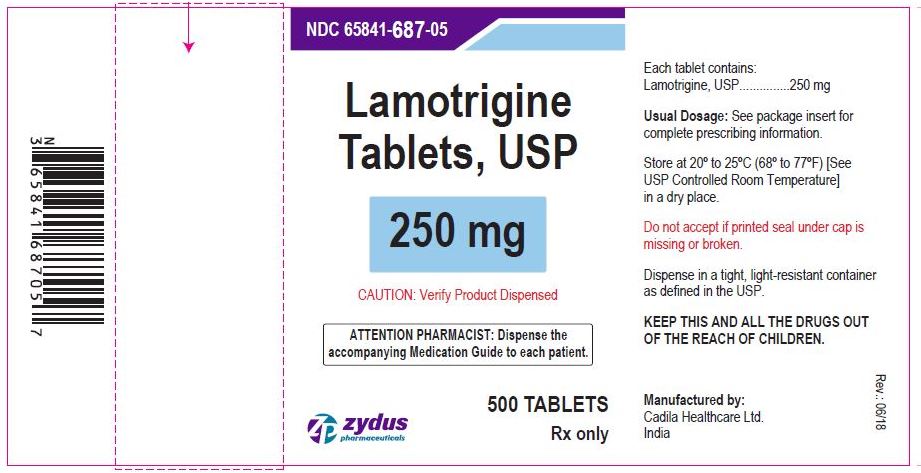 DRUG LABEL: Lamotrigine
NDC: 65841-682 | Form: TABLET
Manufacturer: Zydus Lifesciences Limited
Category: prescription | Type: HUMAN PRESCRIPTION DRUG LABEL
Date: 20251004

ACTIVE INGREDIENTS: LAMOTRIGINE 25 mg/1 1
INACTIVE INGREDIENTS: LACTOSE MONOHYDRATE; MAGNESIUM STEARATE; SODIUM STARCH GLYCOLATE TYPE A POTATO; POVIDONE; CELLULOSE, MICROCRYSTALLINE

LAMOTRIGINE TABLETS and LAMOTRIGINE TABLETS (CHEWABLE, DISPERSIBLE).

PACKAGE LABEL.PRINCIPAL DISPLAY PANEL

Lamotrigine Tablets (Chewable, Dispersible), 5 mg

NDC 65841-689-01 in bottle of 100 tablets

100 tablets

Rx only

Lamotrigine Tablets (Chewable, Dispersible), 5 mg

Lamotrigine Tablets (Chewable, Dispersible), 25 mg

NDC 65841-690-01 in bottle of 100 tablets

100 tablets

Rx only

Lamotrigine Tablets (Chewable, Dispersible), 25 mg

Lamotrigine Tablets USP, 25 mg

NDC 65841-682-01 in bottle of 100 tablets

100 tablets

Rx only

Lamotrigine Tablets USP, 25 mg

Lamotrigine Tablets USP, 50 mg

NDC 65841-683-01 in bottle of 100 tablets

100 tablets

Rx only

Lamotrigine Tablets USP, 50 mg

Lamotrigine Tablets USP, 100 mg

NDC 65841-684-01 in bottle of 100 tablets

100 tablets

Rx only

Lamotrigine Tablets USP, 100 mg

Lamotrigine Tablets USP, 150 mg

NDC 65841-685-14 in bottle of 60 tablets

60 tablets

Rx only

Lamotrigine Tablets USP, 150 mg

Lamotrigine Tablets USP, 200 mg

NDC 65841-686-14 in bottle of 60 tablets

60 tablets

Rx only

Lamotrigine Tablets USP, 200 mg

Lamotrigine Tablets USP, 250 mg

NDC 65841-687-05 in bottle of 500 tablets

500 tablets

Rx only

Lamotrigine Tablets USP, 250 mg